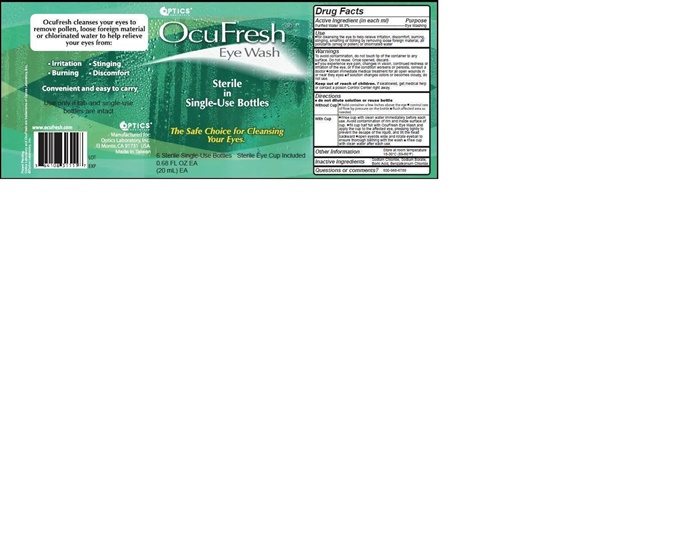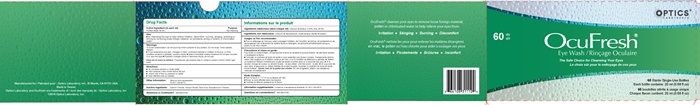 DRUG LABEL: OCUFRESH
NDC: 64108-313 | Form: LIQUID
Manufacturer: Optics Laboratory Inc.
Category: otc | Type: HUMAN OTC DRUG LABEL
Date: 20251229

ACTIVE INGREDIENTS: WATER 0.988 mL/1 mL
INACTIVE INGREDIENTS: SODIUM CHLORIDE; SODIUM BORATE; BORIC ACID; benzalkonium chloride

OCUFRESH (water) liquid

Drug Facts Active Ingredient (in each ml)

PURIFIED WATER 98.8%

Purpose

Eye Washing

Use:

- for cleaning the eye to help relieve irritation, discomfort, burning, stinging, smarting or itching by removing loose foreign material, air pollutants (smog or pollen) or chlorinated water.

Warnings:

To avoid contamination, do not touch tip of the container to any surface. Do not reuse. Onced open, discard.

- if you experience eye pain, changes in vision, continued redness or irritation of the eye, or if the condition worsens or persists, consult a doctor
- obtain immediate medical treatment for all open wounds in or near the eye
- if solution changes colors or becomes cloudy, do not use.

Keep out of reach of children. If swallowed, get medical help or contact a poison Control Center right away.

Directions:

- do not dilute solution or reuse bottle
- hold container a few inches above the eye
- control rate of flow by pressure on bottle
- flush affected area as needed

Without Cup

- hold container a few inches above the eye
- control rate of flow by pressure on bottle
- flush affected area as needed

With Cup

- rinse cup with clean water immediately before each use. Avoid contamination of rim and inside surfaceof cup
- fill cup half full with OcuFresh Eye Wash and apply the cup to the affected eye , pressing tightly to prevent escape of the liquid, and tilt the head backward
- open eyelids wide and rotate eyeball to ensure thorough bathing with the wash
- rinse cup with clean water after each use

Other Information:

Store at room temperature

15-30°C (59-86°F)

Inactive Ingredients:

Sodium Chloride, Sodium Borate, Boric Acid, benzalkonium Chloride

Questions or Comments?

800-968-6788

OcuFresh product label

OPTICS®

Laboratory

OcuFresh®

Eye Wash

The Safe Choice for Cleansing Your Eyes

60 Sterile Single-Use Bottles

Each bottle contains: 20 ml (0.68 fl oz)

OcuFresh® cleanses your eyes to remove loose foreign material, pollen or chlorinated water to help relieve your eyes from:

Irritation • Stinging • Burning • Discomfort

Manufactured for: Optics Laboratory, Inc., El Monte, CA 91731 USA

Made ib Taiwan

Optics Laboratory and ocufresh are trademarksof: Optics Laboratory, inc

©2015 Optics Laboratory, Inc.

OPTICS®

Laboratory

OcuFresh®

Eye Wash

Sterile in Single-Use Bottles

The Safe Choice for Cleansing Your Eyes

6 Sterile Single-Use Bottles Sterile Eye Cup Included

Convenient and easy to carry

Use only if tab and single-use bottles are intact

res